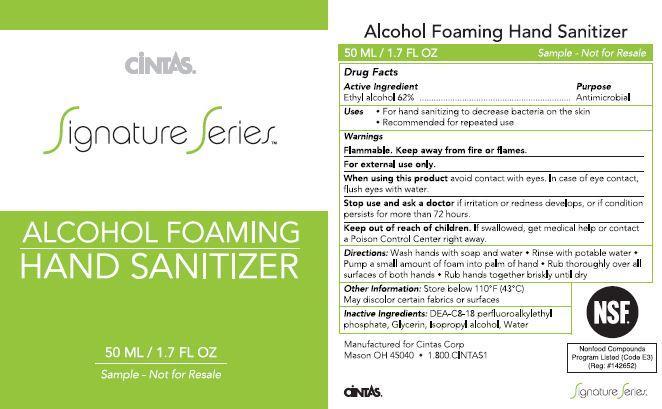 DRUG LABEL: Signature Alcohol Foaming Hand Sanitizer
NDC: 42961-013 | Form: LIQUID
Manufacturer: Cintas Corp.
Category: otc | Type: HUMAN OTC DRUG LABEL
Date: 20160308

ACTIVE INGREDIENTS: ALCOHOL 62 mL/100 mL
INACTIVE INGREDIENTS: DIETHANOLAMINE BIS(C8-C18 PERFLUOROALKYLETHYL)PHOSPHATE; GLYCERIN; ISOPROPYL ALCOHOL; WATER

Drug Facts

Active Ingredient

Ethyl alcohol 62%

Purpose

Antimicrobial

Uses

For hand sanitizing to decrease bacteria on the skin

Recommended for repeated use

Warnings

Flammable. Keep away from fire or flames.

For external use only.

When using this product avoid contact with eyes. In case of eye contact, flush eyes with water.

Stop use and ask a doctor if irritation or redness develops, or if condition persists for more than 72 hours.

Keep out of reach of children.

If swallowed, get medical help or contact a Poison Control Center right away.

Directions:

Wash hands with soap and water

Rinse with potable water

Pump a small amount of foam into palm of hand

Rub thoroughly over all surfaces of both hands

Rub hands together briskly until dry

Other Information:

Store below 110 F (43 C)

May discolor certain fabrics or surfaces

Inactive Ingredients:

DEA-C8-18 perfluoroalkylethyl phosphate, Glycerin, Isopropyl alcohol, Water

PACKAGE LABEL

Cintas

Signature Series

Alcohol Foaming

Hand Sanitizer

50 ML/1.7 FL OZ

Sample - Not for Resale